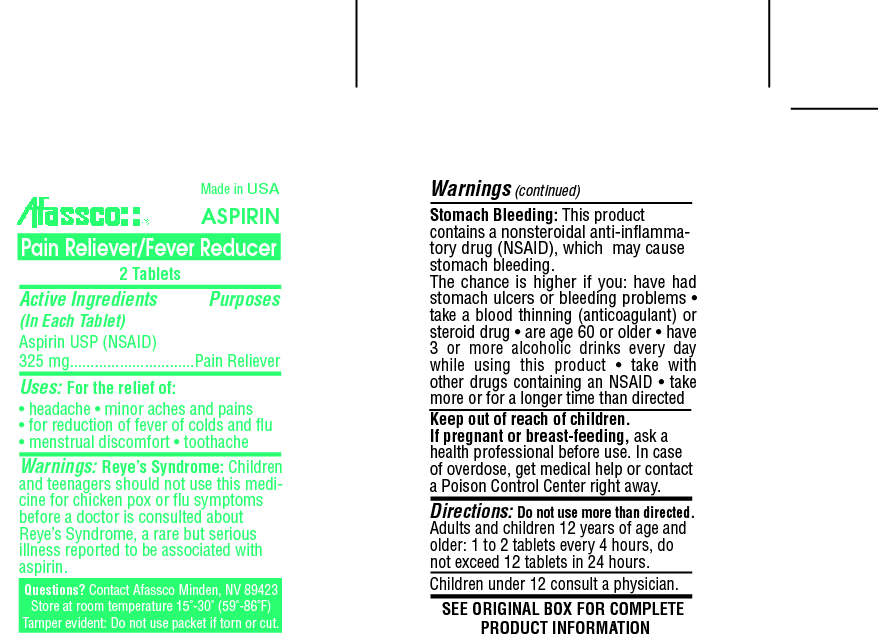 DRUG LABEL: Aspirin 325mg
NDC: 51532-0232 | Form: TABLET
Manufacturer: Afassco Inc.
Category: otc | Type: HUMAN OTC DRUG LABEL
Date: 20190921

ACTIVE INGREDIENTS: ASPIRIN 325 mg/1 1
INACTIVE INGREDIENTS: POVIDONE K30; MICROCRYSTALLINE CELLULOSE; STARCH, CORN

ACTIVE INGREDIENT

Aspirin USP (NSAID) 325 mg

PURPOSE

Pain Reliever

Uses:

For the relief of:

• headache • minor aches and pains

• for reduction of fever of colds and flu

• menstrual discomfort • toothache

Warnings:

Reye’s Syndrome:

Children and teenagers should not use this medicine for chicken pox or flu symptoms before a doctor is consulted about Reye’s Syndrome, a rare but serious illness reported to be associated with aspirin.

Stomach Bleeding:

This product contains a nonsteroidal anti-inflammatory drug (NSAID), which may cause stomach bleeding.The chance is higher if you: have had stomach ulcers or bleeding problems • take a blood thinning (anticoagulant) or steroid drug • are age 60 or older • have 3 or more alcoholic drinks every day while using this product • take with other drugs containing an NSAID • take more or for a longer time than directed

Keep out of reach of children.

PREGNANCY OR BREAST FEEDING

If pregnant or breast-feeding, ask a health professional before use.

OVERDOSAGE

In case of overdose, get medical help or contact a Poison Control Center right away.

Directions:

Do not use more than directed.

Adults and children 12 years of age and older: 1 to 2 tablets every 4 hours, do not exceed 12 tablets in 24 hours.

Children under 12 consult a physician.

INACTIVE INGREDIENT

SEE ORIGINAL BOX FOR COMPLETE

PRODUCT INFORMATION

PACKAGE LABEL

res